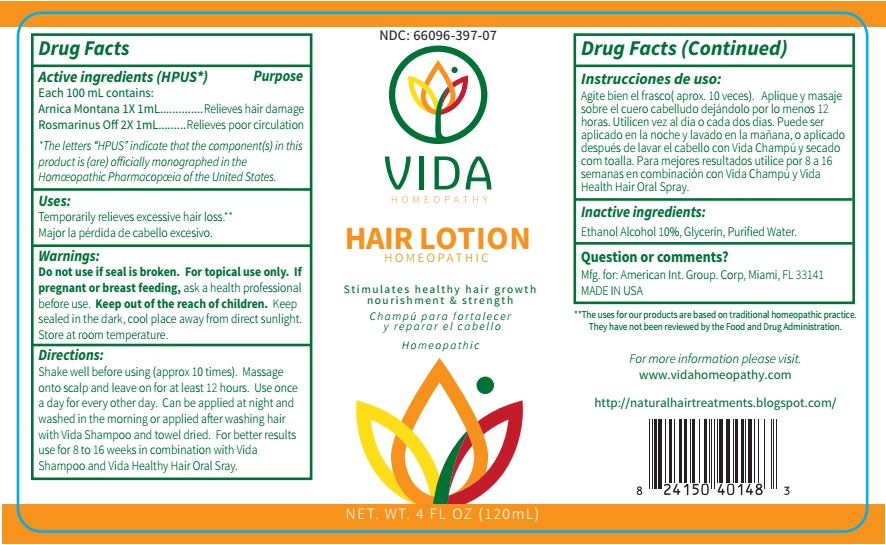 DRUG LABEL: Vida Hair
NDC: 66096-397 | Form: LOTION
Manufacturer: OHM PHARMA INC.
Category: homeopathic | Type: HUMAN OTC DRUG LABEL
Date: 20190905

ACTIVE INGREDIENTS: ARNICA MONTANA 1 [hp_X]/120 mL; ROSMARINUS OFFICINALIS FLOWERING TOP 2 [hp_X]/120 mL
INACTIVE INGREDIENTS: ALCOHOL; GLYCERIN; WATER

Vida Hair Lotion

Active ingerdients (HPUS*) Purpose

Each 100 mL contains:

Arnica Montana 1X 1mL...........................................Relieves hair damage

Rosmarinus Off 2X 1mL........................................Relieves poor circulation

*The letters *HPUS* indicate that the component(s) in this product is (are) officially monographed in the Homeopathic Pharmacopeia of the United States.

INDICATIONS AND USAGE

Uses: Temporarily relieves excessive hair loss.**

Major la pérdida de cabello excesivo.

**The uses for our products are based on traditional homeopathic practice. They have not been reviewed by the Food and Drug Administration.

WARNINGS

Warnings: For topical use only. If pregnant or breast feeding, ask a health professional before use. Keep sealed in the dark, cool place away from direct sunlight. Store at room temperature.

- KEEP OUT OF REACH OF CHILDREN.

DOSAGE AND ADMINISTRATION

Directions: Shake well before using (approx 10 times). Massage onto scalp and leave on for at least 12 hours. Use once a day for every other day. Can be applied at night and washed in the morning or applied after washing hair with Vida Shampoo and towel dried. For better results use for 8 to 16 weeks in combination with Vida Shampoo and Vida Healthy Hair Oral Spray.

Instrucciones de uso: Agite bien el frasco (approx. 10 veces). Aplique y masaje sobre el cuero cabelludo dejándolo por lo menos 12 horas. Utilicen vez al dia o cada dos dias. Puede ser aplicado en la noche y lavado en la mañana, o aplicado después de lavar el cabello con Vida Champú y secado com toalla. Para mejores resultados utilice por 8 a 16 semanas en combinación con Vida Champú y Vida Health Hair Oral Spray.

Do not use if seal is broken.

Inactive ingredients: Ethanol Alcohol 10%, Glycerin, Purified Water.

QUESTIONS

Question or comments? Mfg. for: American Int. Group. Corp, Miami, FL 33141

Made in USA

For more information please visit. www.vidahomeopathy.com

http://naturalhairtreatments.blogspot.com/

PACKAGE LABEL

NDC: 66096-397-07

VIDA HOMEOPATHY

HAIR LOTION HOMEOPATHIC

Stimulates healthyhair growth nourishment & strength

Champú para fortalecer y reparar el cabello

Homeopathic

NET. WT. 4 FL OZ (120Ml)

PURPOSE

Healthy hair growth nourishment & strength